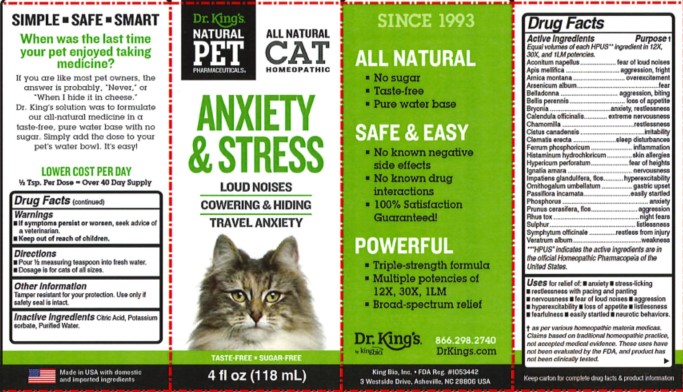 DRUG LABEL: Anxiety and Stress
NDC: 57955-4704 | Form: LIQUID
Manufacturer: King Bio Inc.
Category: homeopathic | Type: OTC ANIMAL DRUG LABEL
Date: 20240716

ACTIVE INGREDIENTS: ACONITUM NAPELLUS WHOLE 12 [hp_X]/118 mL; APIS MELLIFERA 12 [hp_X]/118 mL; ARNICA MONTANA WHOLE 12 [hp_X]/118 mL; ARSENIC TRIOXIDE 12 [hp_X]/118 mL; ATROPA BELLADONNA 12 [hp_X]/118 mL; BELLIS PERENNIS WHOLE 12 [hp_X]/118 mL; BRYONIA ALBA ROOT 12 [hp_X]/118 mL; CALENDULA OFFICINALIS FLOWERING TOP 12 [hp_X]/118 mL; MATRICARIA CHAMOMILLA WHOLE 12 [hp_X]/118 mL; HELIANTHEMUM CANADENSE 12 [hp_X]/118 mL; CLEMATIS RECTA FLOWERING TOP 12 [hp_X]/118 mL; FERROSOFERRIC PHOSPHATE 12 [hp_X]/118 mL; HISTAMINE DIHYDROCHLORIDE 12 [hp_X]/118 mL; HYPERICUM PERFORATUM WHOLE 12 [hp_X]/118 mL; STRYCHNOS IGNATII SEED 12 [hp_X]/118 mL; IMPATIENS GLANDULIFERA FLOWER 12 [hp_X]/118 mL; ORNITHOGALUM UMBELLATUM WHOLE 12 [hp_X]/118 mL; PASSIFLORA INCARNATA FLOWERING TOP 12 [hp_X]/118 mL; PHOSPHORUS 12 [hp_X]/118 mL; PRUNUS CERASIFERA FLOWER 12 [hp_X]/118 mL; TOXICODENDRON PUBESCENS LEAF 12 [hp_X]/118 mL; SULFUR 12 [hp_X]/118 mL; COMFREY ROOT 12 [hp_X]/118 mL; VERATRUM ALBUM ROOT 12 [hp_X]/118 mL
INACTIVE INGREDIENTS: CITRIC ACID MONOHYDRATE; POTASSIUM SORBATE; WATER

Anxiety and Stress

Warnings

- If symptoms persist or worsen, seek advice of a veterinarian.
- Keep out of reach of children.

Directions

- Pour 1/2 measuring teaspoon into fresh water.
- Dosage is for cats of all sizes.

Other Information

Tamper resistant for your protection.

Use only if safety seal is intact.

Keep carton for complete drug facts and product information.

This product has not been clinically tested.

Questions? Call 866.298.2740

King Bio, Inc. 3 Westside Drive

Asheville, NC, 28806 USA

FDA Reg. #1053442

For latest product information and instructions: www.DrKings.com

Keep out of reach of children.

Active Ingredients

Aconitum napellus, Apis mellifica, Arnica montana, Arsenicum album, Belladonna, Bellis perennis, Bryonia, Calendula officinalis, Chamomilla, Cistus canadensis, Clematis erecta, Ferrum phosphoricum, Histaminum hydrochloricum, Hypericum perforatum, Ignatia amara, Impatiens glandulifera, flos, Ornithogalum umbellatum, Passiflora incarnata, Phosphorus, Prunus cerasifera, flos, Rhus tox, Sulphur, Symphytum officinale, veratrum album.

HPUS Indicates the active ingredients are in the official Homeopathic Pharmacopeia of the United States.

Uses

Uses for relief of:

- anxiety
- stress-licking
- restlessness with pacing and panting
- nervousness
- fear of louf noises
- aggression
- hyperexcitability
- loss of appetite
- listlessness
- fearfulness
- easily startled
- neurotic behaviors

As per various homeopathic materia medicas. Claims based on traditional homeopathic pracice, not accepted medical evidence. These uses have not been evaluated by the FDA, and Product has not been clinically tested.

Inactive Ingredient

Citric acid, Potassium sorbate, and Purified water.

PURPOSE

Equal volumes of each HPUS ingredient in 12X, 30X, and 1LM potencies.

Aconitum napellus................................fear of loud noises

Apis mellifica........................................aggression, fright

Arnica montana.......................................overexcitement

Arsenicum album.....................................................fear

Belladonna..........................................aggression, biting

Bellis perennis........................................loss of appetite

Bryonia...........................................anxiety, restlessness

Calendula officinalis.........................extreme nervousness

Chamomilla.................................................restlessness

Cistus canadensis............................................irritability

Clematis erecta...................................sleep disturbances

Ferrum phosphoricum.................................inflammation

Histaminum hydrochloricum.........................skin allergies

Hypericum perforatum...............................fear of heights

Ignatia amara..............................................nervousness

Impatiens glandulifera, flos......................hyperexcitability

Ornithogalum umbellatum............................gastric upset

Passiflora incarnata...................................easily startled

Phosphorus.......................................................anxiety

Prunus cerasifera, flos...................................aggression

Rhus tox......................................................night fears

Sulphur.......................................................listlessness

Symphytum officinale.........................restless from injury

Veratrum album.............................................weakness